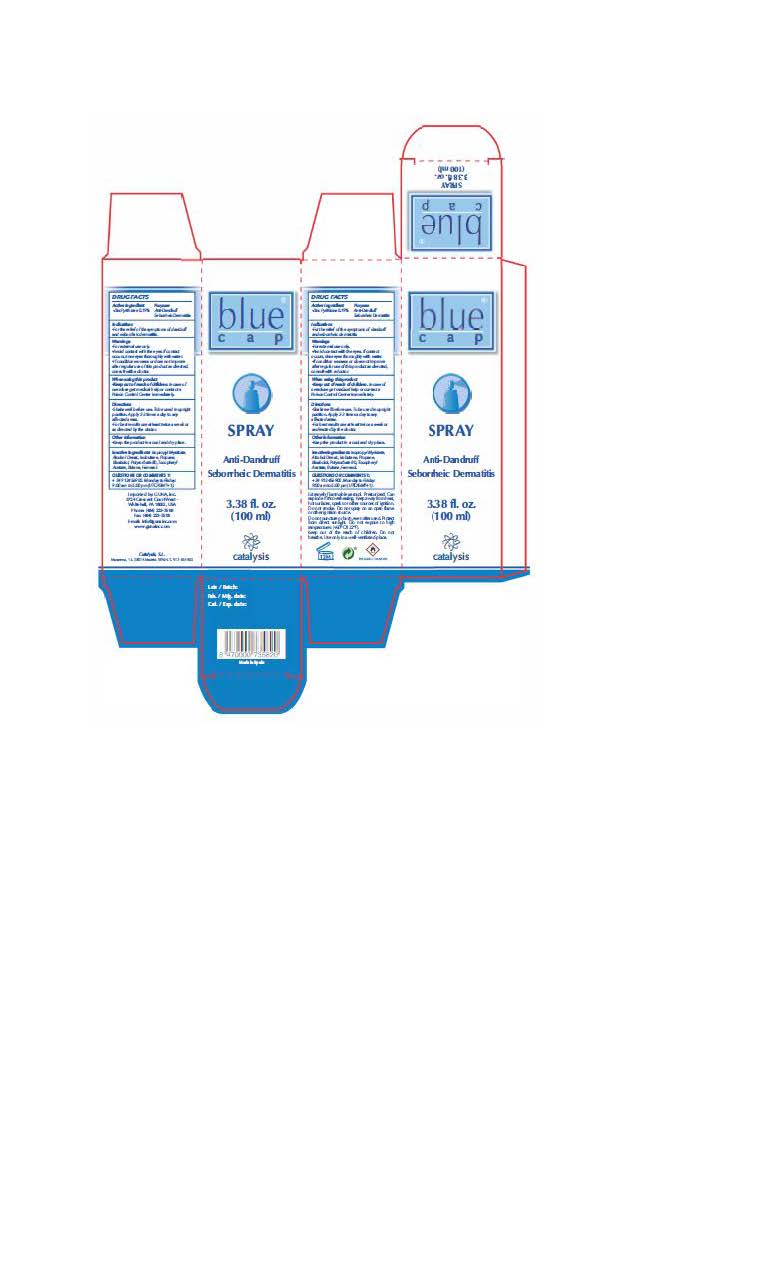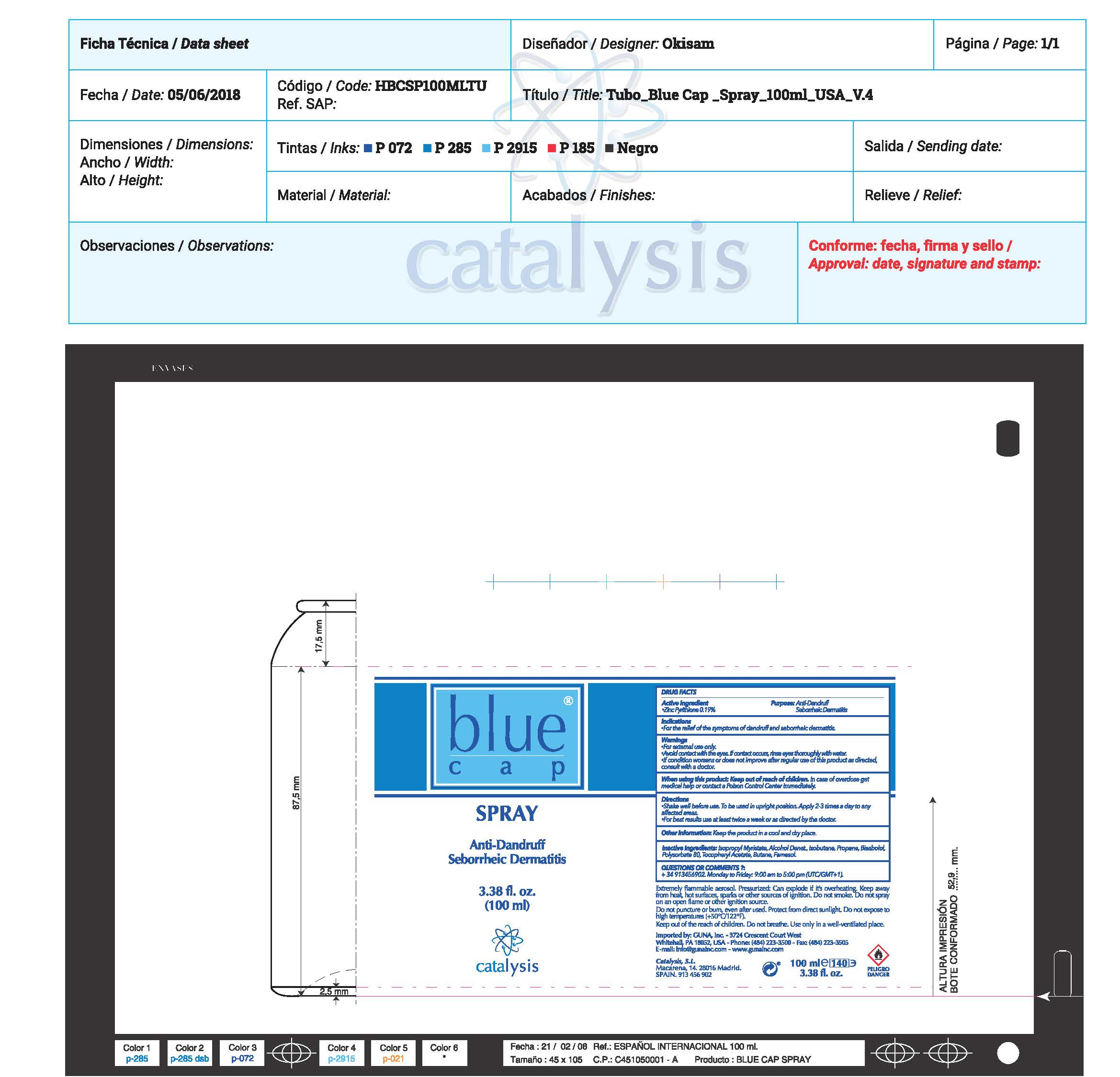 DRUG LABEL: Blue Cap
NDC: 64539-021 | Form: SPRAY
Manufacturer: Catalysis, SL
Category: otc | Type: HUMAN OTC DRUG LABEL
Date: 20180913

ACTIVE INGREDIENTS: PYRITHIONE ZINC 0.19 mg/1 mL
INACTIVE INGREDIENTS: ALCOHOL; FARNESOL; PROPANE; ISOBUTANE; ISOPROPYL MYRISTATE; POLYSORBATE 80; .ALPHA.-TOCOPHEROL ACETATE; LEVOMENOL; BUTANE

Blue Cap Spray

ACTIVE INGREDIENTS PURPOSE

Pyrithione Zinc 0.19%.................. Antidandruff/ Seborrheic Dermatitis

Warnings

- For external use only.
- Avoid contact with the eyes. If contact occurs, rinse throughly with water
- If conditions worsens or does not improve after regular use of this product as directed, consult with a doctor
- When using this product KEEP out of the reach of children. In case of overdose get medical help or contact a Poison Center inmediately

WARNINGS

- For external use only.
- Avoid contact with the eyes. If contact occurs, rinse throughly with water
- If conditions worsens or does not improve after regular use of this product as directed, consult with a doctor
- When using this product KEEP out of the reach of children. In case of overdose get medical help or contact a Poison Center inmediately

Warnings

Keep out of reach of children

Questions or comments?

+ 34 91 345 6902 M-F 9:00 am to 5:00 pm

Other Information

. keep the product in a cool and dry place

Directions

- Shake well before use. To be use in upright position. Apply 2-3 times a day to any affected area.
- For best results use at least twice a week or as directed by the doctor

DOSAGE AND ADMINISTRATION

- Shake well before use. To be use in upright position. Apply 2-3 times a day to any affected area.
- For best results use at least twice a week or as directed by the doctor

Uses

- For the relief of the symptons of dandruff and seborrheic dermatitis

Inactive Ingredients

Isopropyl Myristate, Alcohol, Isobutane, Propane. Bisabolol, Polysorbate 80, Zinc Pyrithione, Butane, Tocopheryl Acetate, Farnesol

Uses

- For the relief of the symptons of dandruff and seborrheic dermatitis